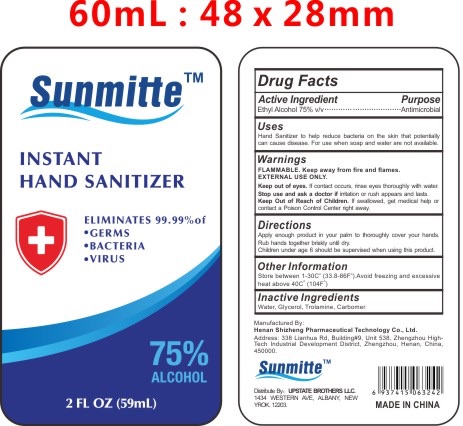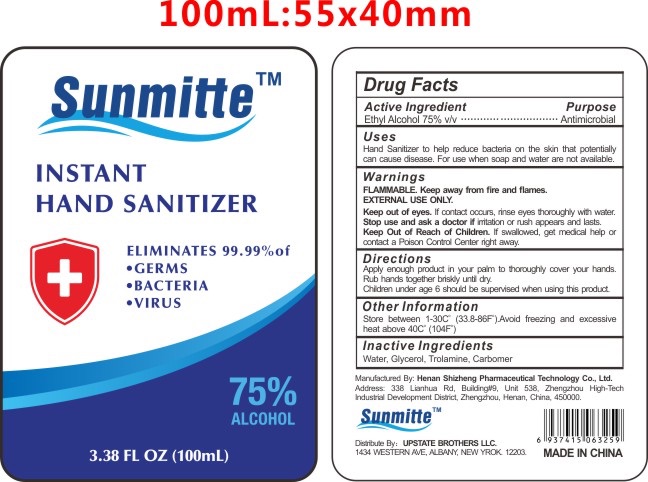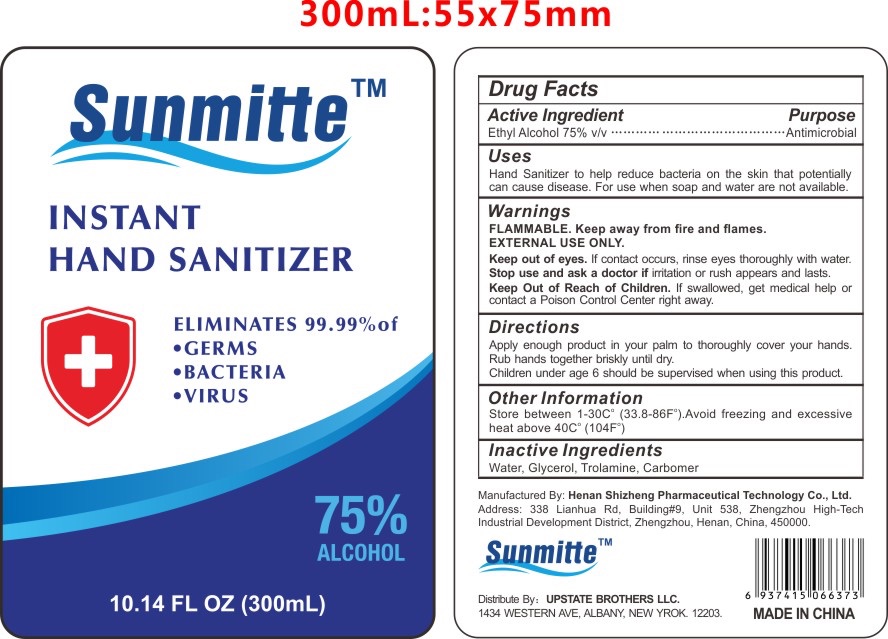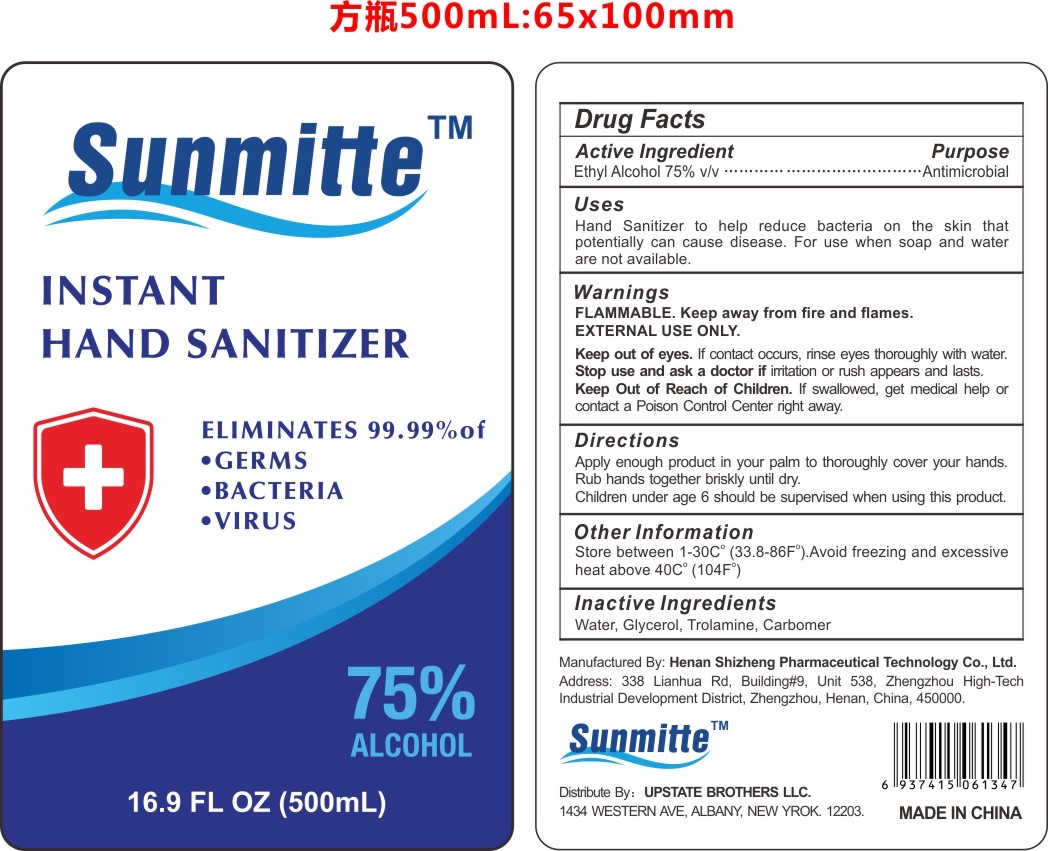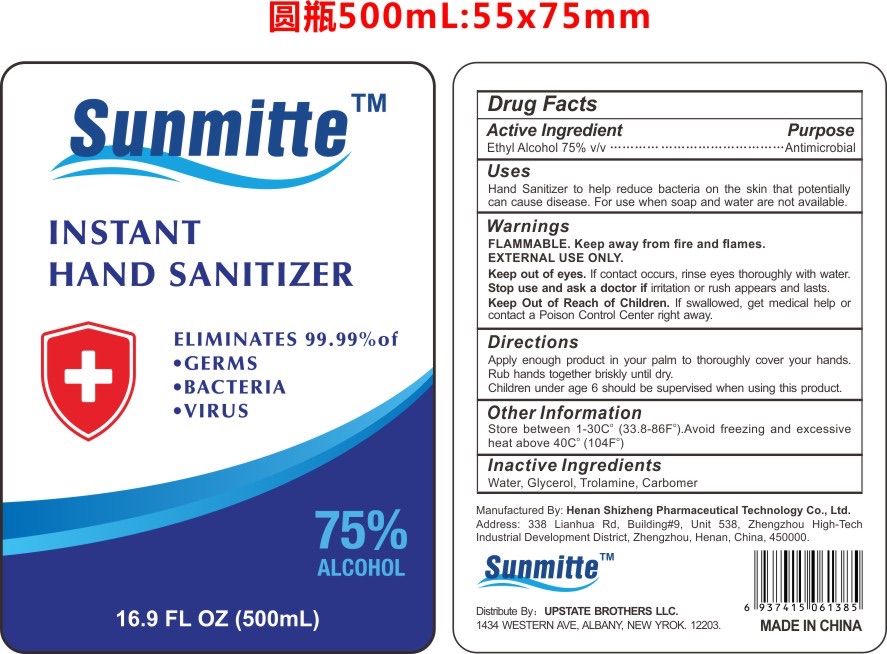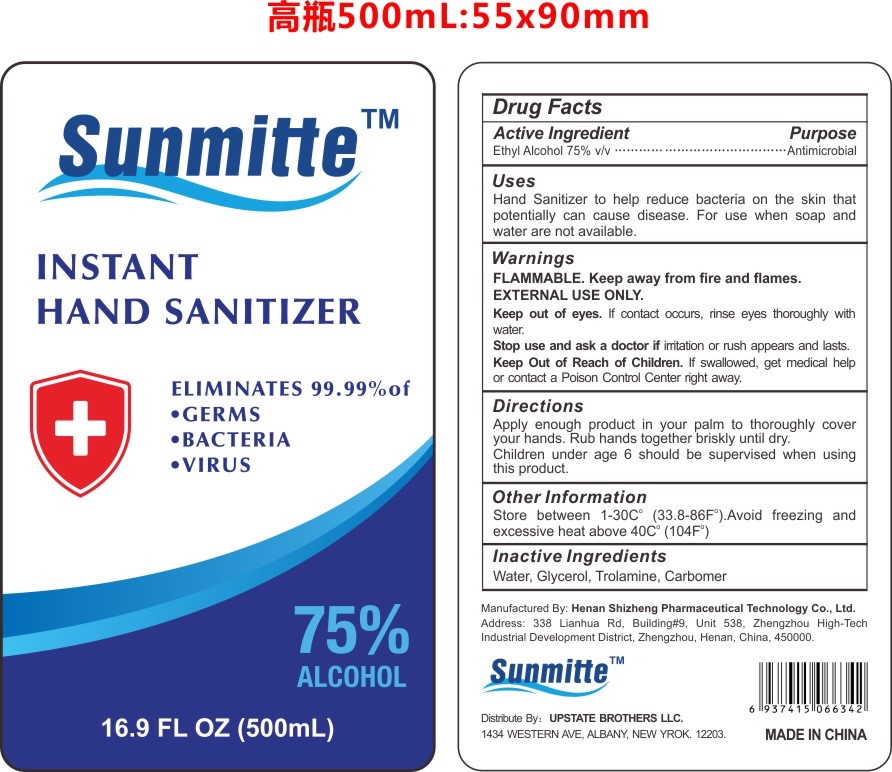 DRUG LABEL: Sunmitte Hand Sanitizer
NDC: 75138-120 | Form: GEL
Manufacturer: Henan Shizheng Pharmaceutical Technology Co., Ltd.
Category: otc | Type: HUMAN OTC DRUG LABEL
Date: 20200426

ACTIVE INGREDIENTS: ALCOHOL 75 mL/100 mL
INACTIVE INGREDIENTS: TROLAMINE 0.2 mL/100 mL; GLYCERIN 3 mL/100 mL; CARBOMER HOMOPOLYMER, UNSPECIFIED TYPE 0.8 mL/100 mL; WATER 21 mL/100 mL

Sunmitte Hand Sanitizer Product Listing

This is a hand sanitizer manufactured according to the Temporary Policy for Preparation of Certain Alcohol-Based Hand Sanitizer Products During the Public Health Emergency (CoViD-19); Guidance for Industry.

The hand sanitizer is manufactured using only the following United States Pharmacopoeia (USP) grade ingredients in the preparation of the product (percentage in final product formulation) consistent with World Health Organization (WHO) recommendations:

1. Alcohol (75%, v/v) in an aqueous solution denatured according to Alcohol and Tobacco Tax and Trade Bureau regulations in 27 CFR part 20.
2. Glycerin(3% v/v).
3. Carbomer(0.8% v/v).
4. Trolamine(0.2% v/v).
5. Sterile distilled water or boiled cold water.

The firm does not add other active or inactive ingredients. Different or additional ingredients may impact the quality and potency of the product.

Active Ingredient(s)

Isopropyl Alcohol 75% v/v. Purpose: Antiseptic

Purpose

Antiseptic, Hand Sanitizer

Use

Hand Sanitizer to help reduce bacteria that potentially can cause disease. For use when soap and water are not available.

Warnings

For external use only. Flammable. Keep away from heat or flame

When using this product keep out of eyes, ears, and mouth. In case of contact with eyes, rinse eyes thoroughly with water.
Stop use and ask a doctor if irritation or rash occurs. These may be signs of a serious condition.
Keep out of reach of children. If swallowed, get medical help or contact a Poison Control Center right away.

Stop use and ask a doctor if irritation or rash occurs and lasts.

Keep out of reach of children. If swallowed, get medical help or contact a Poison Control Center right away.

Directions

- Apply enough product in your palm to thoroughly cover your hands. Rub hands together briskly until dry.
- Children under age 6 should be supervised when using this product.

Other information

- Store between 1-30C (33.8-86F)
- Avoid freezing and excessive heat above 40C (104F)

Inactive ingredients

glycerin, carbomer, water, Trolamine

Package Label - Principal Display Panel

59 ml NDC: 75138-120-06

100 ml NDC: 75138-120-10

300 ml NDC: 75138-120-30

500 ml NDC: 75138-120-50

500 ml NDC: 75138-120-51

500 ml NDC: 75138-120-52